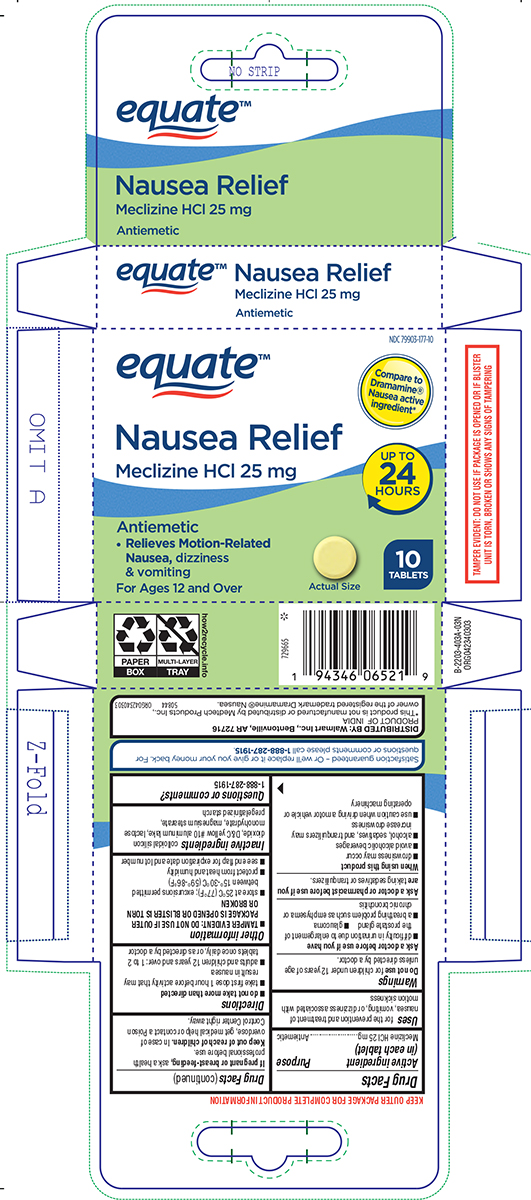 DRUG LABEL: Nausea Relief
NDC: 79903-177 | Form: TABLET
Manufacturer: WALMART INC.
Category: otc | Type: HUMAN OTC DRUG LABEL
Date: 20250808

ACTIVE INGREDIENTS: MECLIZINE HYDROCHLORIDE 25 mg/1 1
INACTIVE INGREDIENTS: SILICON DIOXIDE; D&C YELLOW NO. 10 ALUMINUM LAKE; LACTOSE MONOHYDRATE; MAGNESIUM STEARATE; STARCH, CORN

Equate 44-403A-N

Active ingredient (in each tablet)

Meclizine HCl 25 mg

Purpose

Antiemetic

Uses

for the prevention and treatment of nausea, vomiting, or dizziness associated with motion sickness

Warnings

Do not use

for children under 12 years of age unless directed by a doctor.

Ask a doctor before use if you have

- difficulty in urination due to enlargement of the prostate gland
- glaucoma
- a breathing problem such as emphysema or chronic bronchitis

Ask a doctor or pharmacist before use if you are

taking sedatives or tranquilizers.

When using this product

- drowsiness may occur
- avoid alcoholic beverages
- alcohol, sedatives, and tranquilizers may increase drowsiness
- use caution when driving a motor vehicle or operating machinery

If pregnant or breast-feeding,

ask a health professional before use.

Keep out of reach of children.

In case of overdose, get medical help or contact a Poison Control Center right away.

Directions

- do not take more than directed
- take first dose 1 hour before activity that may result in nausea
- adults and children 12 years and over: 1 to 2 tablets once daily, or as directed by a doctor

Other information

- TAMPER EVIDENT: DO NOT USE IF OUTER PACKAGE IS OPENED OR BLISTER IS TORN OR BROKEN
- store at 25°C (77°F); excursions permitted between 15°-30°C (59°-86°F)
- protect from heat and humidity
- see end flap for expiration date and lot number

Inactive ingredients

colloidal silicon dioxide, D&C yellow #10 aluminum lake, lactose monohydrate, magnesium stearate, pregelatinized starch

Questions or comments?

1-888-287-1915

Principal display panel

equate™

NDC 79903-177-10

Compare to
Dramamine®
Nausea active
ingredient*

Nausea Relief
Meclizine HCl 25 mg

Antiemetic

• Relieves Motion-Related
Nausea, dizziness
& vomiting

For Ages 12 Years and Over

UP TO
24
HOURS

Actual Size

10
TABLETS

TAMPER EVIDENT: DO NOT USE IF PACKAGE IS OPENED OR IF BLISTER
UNIT IS TORN, BROKEN OR SHOWS ANY SIGNS OF TAMPERING

Satisfaction guaranteed - Or we'll replace it or give you your money back. For
questions or comments please call 1-888-287-1915.

DISTRIBUTED BY: Walmart Inc., Bentonville, AR 72716
PRODUCT OF INDIA
*This product is not manufactured or distributed by Medtech Products Inc.,
owner of the registered trademark Dramamine® Nausea. 50844 ORG042340303

Equate 44-403N